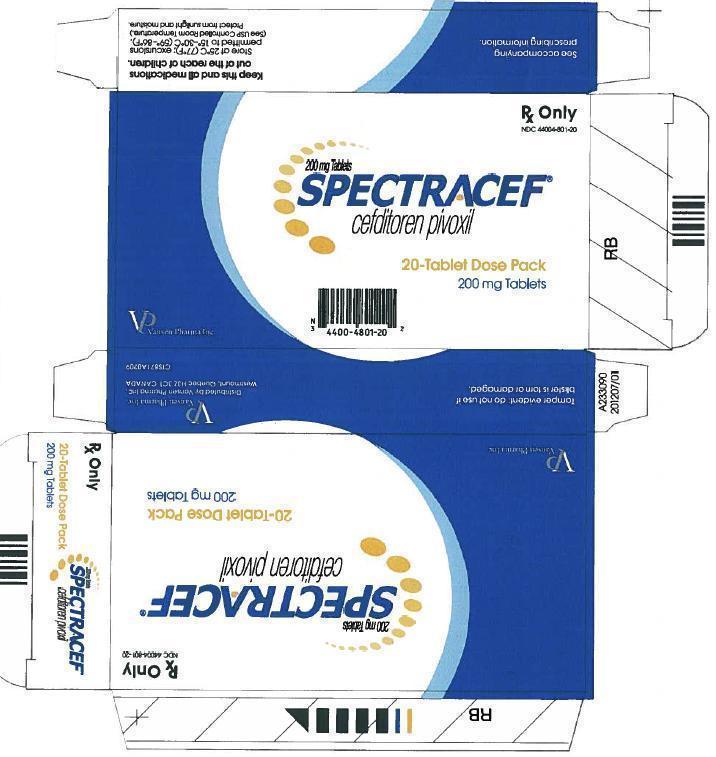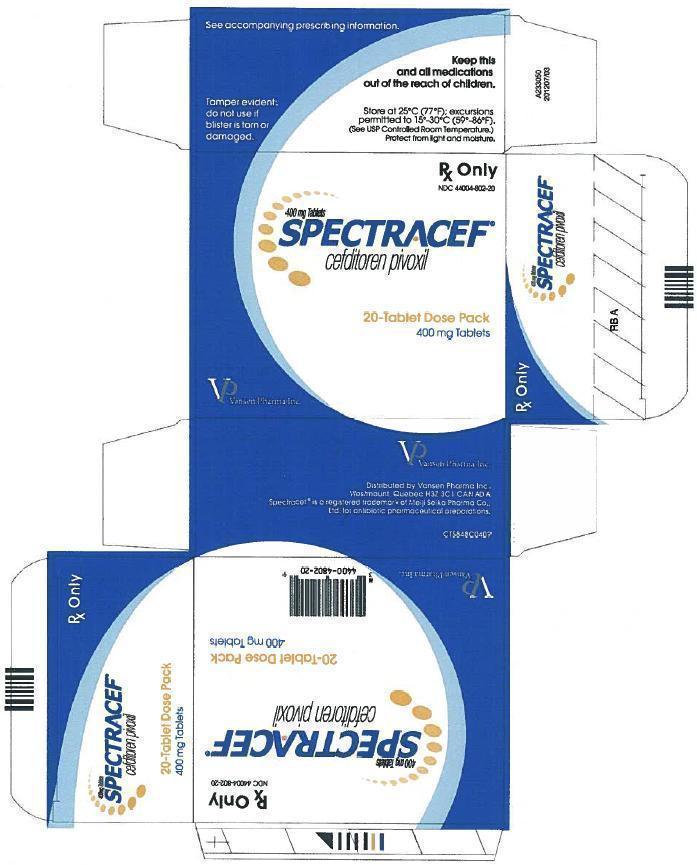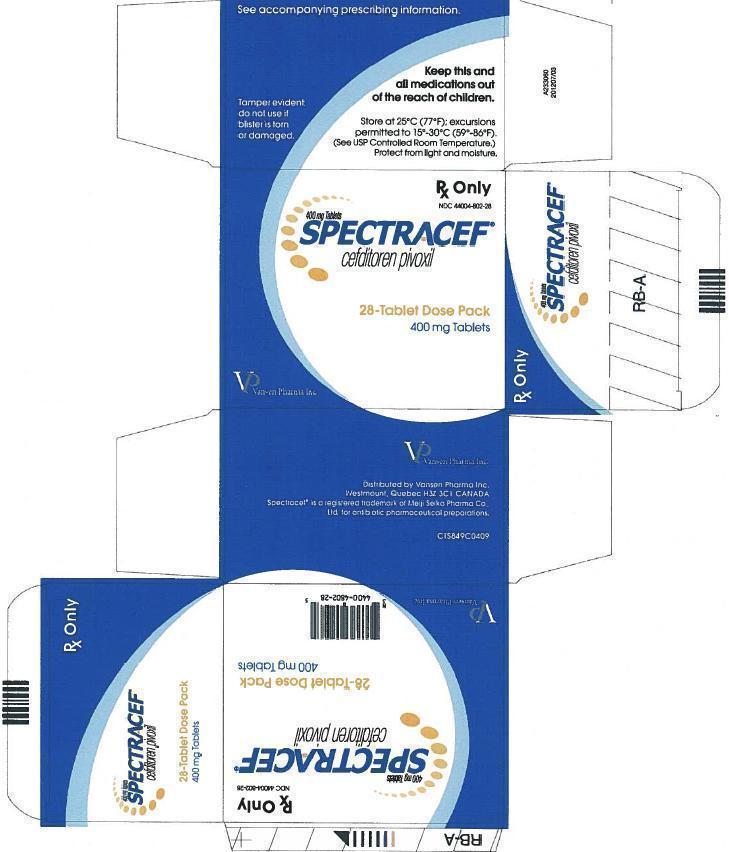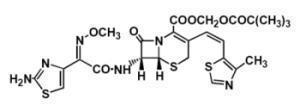 DRUG LABEL: Spectracef
NDC: 44004-801 | Form: TABLET, FILM COATED
Manufacturer: Vansen Pharma Inc.
Category: prescription | Type: HUMAN PRESCRIPTION DRUG LABEL
Date: 20130604

ACTIVE INGREDIENTS: CEFDITOREN PIVOXIL 200 mg/1 1
INACTIVE INGREDIENTS: CARNAUBA WAX; CROSCARMELLOSE SODIUM; D&C RED NO. 27; MANNITOL; HYDROXYPROPYL CELLULOSE; HYPROMELLOSES; MAGNESIUM STEARATE; POLYETHYLENE GLYCOLS; PROPYLENE GLYCOL; SHELLAC; SODIUM CASEINATE; SODIUM TRIPOLYPHOSPHATE; TITANIUM DIOXIDE; FD&C BLUE NO. 1

Spectracef® (cefditoren pivoxil) Tablets 200 mg and 400 mg

Spectracef® (cefditoren pivoxil) Tablets 200 mg and 400 mg

To reduce the development of drug-resistant bacteria and maintain the effectiveness of SPECTRACEF® and other antibacterial drugs, SPECTRACEF® should be used only to treat infections that are proven or strongly suspected to be caused by bacteria.

DESCRIPTION

SPECTRACEF® tablets contain cefditoren pivoxil, a semi-synthetic cephalosporin antibiotic for oral administration. It is a prodrug which is hydrolyzed by esterases during absorption, and the drug is distributed in the circulating blood as active cefditoren.

Chemically, cefditoren pivoxil is (-)-(6R,7R)-2,2-dimethylpropionyloxymethyl 7-[(Z)-2-(2-aminothiazol-4-yl)-2-methoxy-iminoacetamido]-3-[(Z)-2-(4-methylthiazol-5-yl)ethenyl]-8-oxo-5-thia-1-azabicyclo[4.2.0]oct-2-ene-2-carboxylate. The empirical formula is C25H28N6O7S3 and the molecular weight is 620.73. The structural formula of cefditoren pivoxil is shown below:

cefditoren pivoxil
cefditoren pivoxil

The amorphous form of cefditoren pivoxil developed for clinical use is a light yellow powder. It is freely soluble in dilute hydrochloric acid and soluble at levels equal to 6.06 mg/mL in ethanol and <0.1 mg/mL in water.

SPECTRACEF® (cefditoren pivoxil) tablets contain 200 mg or 400 mg of cefditoren as cefditoren pivoxil and the following inactive ingredients: croscarmellose sodium, mannitol, magnesium stearate, sodium caseinate (a milk protein), and sodium tripolyphosphate. The tablet coating contains hydroxypropyl cellulose carnauba wax, polyethylene glycol, and titanium dioxide. Tablets are printed with ink containing opacode blue S-1-10533.

CLINICAL PHARMACOLOGY

Pharmacokinetics

Absorption

Oral Bioavailability

Following oral administration, cefditoren pivoxil is absorbed from the gastrointestinal tract and hydrolyzed to cefditoren by esterases. Maximal plasma concentrations (Cmax) of cefditoren under fasting conditions average 1.8 ± 0.6 µg/mL following a single 200 mg dose and occur 1.5 to 3 hours following dosing.

Less than dose-proportional increases in Cmax and area under the concentration-time curve (AUC) were observed at doses of 400 mg and above. Cefditoren does not accumulate in plasma following twice daily administration to subjects with normal renal function. Under fasting conditions, the estimated absolute bioavailability of cefditoren pivoxil is approximately 14%. The absolute bioavailability of cefditoren pivoxil administered with a low fat meal (693 cal, 14 g fat, 122 g carb, 23 g protein) is 16.1 ± 3.0%.

Food Effect

Administration of cefditoren pivoxil following a high fat meal (858 cal, 64 g fat, 43 g carb, 31 g protein) resulted in a 70% increase in mean AUC and a 50% increase in mean Cmax compared to administration of cefditoren pivoxil in the fasted state. After a high fat meal, the Cmax averaged 3.1 ± 1.0 µg/mL following a single 200 mg dose of cefditoren pivoxil and 4.4 ± 0.9 µg/mL following a 400 mg dose. Cefditoren AUC and Cmax values from studies conducted with a moderate fat meal (648 cal, 27 g fat, 73 g carb, 29 g protein) are similar to those obtained following a high fat meal.

Distribution

The mean volume of distribution at steady state (Vss) of cefditoren is 9.3 ± 1.6 L. Binding of cefditoren to plasma proteins averages 88% from in vitro determinations, and is concentration-independent at cefditoren concentrations ranging from 0.05 to10 µg/mL. Cefditoren is primarily bound to human serum albumin and its binding is decreased when serum albumin concentrations are reduced. Binding to α-1-acid glycoprotein ranges from 3.3 to 8.1%. Penetration into red blood cells is negligible.

Skin blister fluid

Maximal concentrations of cefditoren in suction-induced blister fluid were observed 4 to 6 hours following administration of a 400 mg dose of cefditoren pivoxil with a mean of 1.1 ± 0.42 µg/mL. Mean blister fluid AUC values were 56 ± 15% of corresponding plasma concentrations.

Tonsil tissue

In fasted patients undergoing elective tonsillectomy, the mean concentration of cefditoren in tonsil tissue 2 to 4 hours following administration of a 200 mg dose of cefditoren pivoxil was 0.18 ± 0.07 µg/g. Mean tonsil tissue concentrations of cefditoren were 12 ± 3% of the corresponding serum concentrations.

Cerebrospinal Fluid (CSF)

Data on the penetration of cefditoren into human cerebrospinal fluid are not available.

Metabolism and Excretion

Cefditoren is eliminated from the plasma, with a mean terminal elimination half-life (t1/2) of 1.6 ± 0.4 hours in young healthy adults. Cefditoren is not appreciably metabolized. After absorption, cefditoren is mainly eliminated by excretion into the urine, with a renal clearance of approximately 4-5 L/h. Studies with the renal tubular transport blocking agent probenecid indicate that tubular secretion, along with glomerular filtration is involved in the renal elimination of cefditoren. Cefditoren renal clearance is reduced in patients with renal insufficiency. (See Special Populations, Renal Insufficiency and Hemodialysis.)

Hydrolysis of cefditoren pivoxil to its active component, cefditoren, results in the formation of pivalate. Following multiple doses of cefditoren pivoxil, greater than 70% of the pivalate is absorbed. Pivalate is mainly eliminated (>99%) through renal excretion, nearly exclusively as pivaloylcarnitine. Following a 200 mg BID regimen for 10 days, the mean decrease in plasma concentrations of total carnitine was 18.1 ± 7.2 nmole/mL, representing a 39% decrease in plasma carnitine concentrations. Following a 400 mg BID regimen for 14 days, the mean decrease in plasma concentrations of carnitine was 33.3 ± 9.7 nmole/mL, representing a 63% decrease in plasma carnitine concentrations. Plasma concentrations of carnitine returned to the normal control range within 7 to 10 days after discontinuation of cefditoren pivoxil. (See PRECAUTIONS, General and CONTRAINDICATIONS.)

Special Populations

Geriatric

The effect of age on the pharmacokinetics of cefditoren was evaluated in 48 male and female subjects aged 25 to 75 years given 400 mg cefditoren pivoxil BID for 7 days. Physiological changes related to increasing age increased the extent of cefditoren exposure in plasma, as evidenced by a 26% higher Cmax and a 33% higher AUC for subjects aged ≥ 65 years compared with younger subjects. The rate of elimination of cefditoren from plasma was lower in subjects aged ≥ 65 years, with t1/2 values 16-26% longer than for younger subjects. Renal clearance of cefditoren in subjects aged ≥ 65 years was 20-24% lower than in younger subjects. These changes could be attributed to age-related changes in creatinine clearance. No dose adjustments are necessary for elderly patients with normal (for their age) renal function.

Gender

The effect of gender on the pharmacokinetics of cefditoren was evaluated in 24 male and 24 female subjects given 400 mg cefditoren pivoxil BID for 7 days. The extent of exposure in plasma was greater in females than in males, as evidenced by a 14% higher Cmax and a 16% higher AUC for females compared to males. Renal clearance of cefditoren in females was 13% lower than in males. These differences could be attributed to gender-related differences in lean body mass. No dose adjustments are necessary for gender.

Renal Insufficiency

Cefditoren pharmacokinetics were investigated in 24 adult subjects with varying degrees of renal function following administration of cefditoren pivoxil 400 mg BID for 7 days. Decreased creatinine clearance (CLcr) was associated with an increase in the fraction of unbound cefditoren in plasma and a decrease in the cefditoren elimination rate, resulting in greater systemic exposure in subjects with renal impairment. The unbound Cmax and AUC were similar in subjects with mild renal impairment (CLcr: 50-80 mL/min/1.73 m^2) compared to subjects with normal renal function (CLcr: >80 mL/min/1.73 m^2). Moderate (CLcr: 30-49 mL/min/1.73 m^2) or severe (CLcr: <30 mL/min/1.73 m^2) renal impairment increased the extent of exposure in plasma, as evidenced by mean unbound Cmax values 90% and 114% higher and AUC values 232% and 324% higher than that for subjects with normal renal function. The rate of elimination from plasma was lower in subjects with moderate or severe renal impairment, with respective mean t1/2 values of 2.7 and 4.7 hours. No dose adjustment is necessary for patients with mild renal impairment (CLcr: 50-80 mL/min/1.73 m^2). It is recommended that not more than 200 mg BID be administered to patients with moderate renal impairment (CLcr: 30-49 mL/min/1.73 m^2) and 200 mg QD be administered to patients with severe renal impairment (CLcr: <30 mL/min/1.73 m^2). (See DOSAGE AND ADMINISTRATION.)

Hemodialysis

Cefditoren pharmacokinetics investigated in six adult subjects with end-stage renal disease (ESRD) undergoing hemodialysis given a single 400 mg dose of cefditoren pivoxil were highly variable. The mean t1/2 was 4.7 hours and ranged from 1.5 to 15 hours. Hemodialysis (4 hours duration) removed approximately 30% of cefditoren from systemic circulation but did not change the apparent terminal elimination half-life. The appropriate dose for ESRD patients has not been determined. (See DOSAGE AND ADMINISTRATION.)

Hepatic Disease

Cefditoren pharmacokinetics were evaluated in six adult subjects with mild hepatic impairment (Child-Pugh Class A) and six with moderate hepatic impairment (Child-Pugh Class B). Following administration of cefditoren pivoxil 400 mg BID for 7 days in these subjects, mean Cmax and AUC values were slightly (<15%) greater than those observed in normal subjects. No dose adjustments are necessary for patients with mild or moderate hepatic impairment (Child-Pugh Class A or B). The pharmacokinetics of cefditoren in subjects with severe hepatic impairment (Child-Pugh Class C) have not been studied.

Microbiology

Cefditoren is a cephalosporin with antibacterial activity against gram-positive and gram-negative pathogens. The bactericidal activity of cefditoren results from the inhibition of cell wall synthesis via affinity for penicillin-binding proteins (PBPs).

Cefditoren is stable in the presence of a variety of ß-lactamases, including penicillinases and some cephalosporinases. Cefditoren has been shown to be active against most strains of the following bacteria, both in vitro and in clinical infections, as described in the INDICATIONS AND USAGE section.

Aerobic Gram-Positive Microorganisms

Staphylococcus aureus (methicillin-susceptible strains, including ß-lactamase-producing strains)

Note: Cefditoren is inactive against methicillin-resistant Staphylococcus aureus

Streptococcus pneumoniae (penicillin-susceptible strains only)

Streptococcus pyogenes

Aerobic Gram-Negative Microorganisms

Haemophilus influenzae (including ß-lactamase-producing strains)

Haemophilus parainfluenzae (including ß-lactamase-producing strains)

Moraxella catarrhalis (including ß-lactamase-producing strains)

The following in vitro data are available, but their clinical significance is unknown. Cefditoren exhibits in vitro minimum inhibitory concentrations (MICs) of ≤0.125 µg/mL against most (≥90%) strains of the following bacteria; however, the safety and effectiveness of cefditoren in treating clinical infections due to these bacteria have not been established in adequate and well-controlled clinical trials.

Aerobic Gram-Positive Microorganisms

Streptococcus agalactiae

Streptococcus Groups C and G

Streptococcus, viridans group (penicillin-susceptible and -intermediate strains)

Susceptibility Tests

Dilution Techniques

Quantitative methods that are used to determine MICs provide reproducible estimates of the susceptibility of bacteria to antimicrobial compounds. The MICs should be determined using a standardized procedure. Standardized procedures are based on dilution methods^1 (broth) or equivalent with standardized inoculum concentrations and standardized concentrations of cefditoren powder. The MIC values obtained should be interpreted according to the following criteria:

For testing Haemophilus spp.a and Streptococcus spp. including S. pneumoniaeb:

Clinical Isolates | MIC (μg/mL) | Interpretation
S. pneumoniae | ≤0.125; 0.250; ≥0.50 | Susceptible (S); Intermediate (I); Resistant (R)
Haemophilus spp. | ≤0.125; 0.250; ≥0.50 | Susceptible (S); Intermediate (I); Resistant (R)
S. pyogenes | ≤0.125 | Susceptible (S)

aThis interpretive standard is applicable only to broth microdilution susceptibility tests with Haemophilus spp. using Haemophilus Test Medium (HTM).^1

bThese interpretive standards are applicable only to broth microdilution susceptibility tests with Streptococcus spp. using cation-adjusted Mueller-Hinton broth with 2-5% lysed horse blood.^1

Susceptibility test criteria cannot be established for S. aureus

A report of “Susceptible” indicates that the pathogen is likely to be inhibited if the antimicrobial compound in the blood reaches the concentration usually achievable. A report of “Intermediate” indicates that the result should be considered equivocal, and, if the microorganism is not fully susceptible to alternative, clinically feasible drugs, the test should be repeated. This category implies possible clinical applicability in body sites where the drug is physiologically concentrated or in situations where high dosage of drug can be used. This category also provides a buffer zone that prevents small, uncontrolled technical factors from causing major discrepancies in interpretation. A report of “Resistant” indicates that the pathogen is not likely to be inhibited if the antimicrobial compound in the blood reaches the concentration usually achievable and that other therapy should be selected.

Standardized susceptibility test procedures require the use of laboratory control bacterial strains to control the technical aspects of the laboratory procedures. Standard cefditoren powder should provide the following MICs with these quality control strains:

Microorganisms | MIC Ranges (µg/mL)
Streptococcus pneumoniaea ATCC 49619; Haemophilus influenzaeb ATCC 49766; Haemophilus influenzaeb ATCC 49247 | 0.016-0.12; 0.004-0.016; 0.06-0.25

aThis quality control range is applicable to only S. pneumoniae ATCC 49619 tested by a microdilution procedure using cation-adjusted Mueller-Hinton broth with 2-5% lysed horse blood.^1

bThis quality control range is applicable to only H. influenzae ATCC 49247 and ATCC 49766 tested by a microdilution procedure using HTM.^1

INDICATIONS AND USAGE

SPECTRACEF® (cefditoren pivoxil) is indicated for the treatment of mild to moderate infections in adults and adolescents (12 years of age or older) which are caused by susceptible strains of the designated microorganisms in the conditions listed below.

Acute Bacterial Exacerbation of Chronic Bronchitis caused by Haemophilus influenzae (including ß-lactamase-producing strains), Haemophilus parainfluenzae (including ß-lactamase producing strains), Streptococcus pneumoniae (penicillin susceptible strains only), or Moraxella catarrhalis (including ß-lactamase-producing strains).

Community-Acquired Pneumonia caused by Haemophilus influenzae (including ß-lactamase-producing strains), Haemophilus parainfluenzae (including ß-lactamase-producing strains), Streptococcus pneumoniae (penicillin-susceptible strains only), or Moraxella catarrhalis (including ß-lactamase producing strains).

Pharyngitis/Tonsillitis caused by Streptococcus pyogenes. NOTE: SPECTRACEF® is effective in the eradication of Streptococcus pyogenes from the oropharynx. SPECTRACEF® has not been studied for the prevention of rheumatic fever following Streptococcus pyogenes pharyngitis/tonsillitis. Only intramuscular penicillin has been demonstrated to be effective for the prevention of rheumatic fever.

Uncomplicated Skin and Skin-Structure Infections caused by Staphylococcus aureus (including ß-lactamase-producing strains) or Streptococcus pyogenes.

To reduce the development of drug-resistant bacteria and maintain the effectiveness of SPECTRACEF® and other antibacterial drugs, SPECTRACEF® should be used only to treat infections that are proven or strongly suspected to be caused by susceptible bacteria. When culture and susceptibility information are available, they should be considered in selecting or modifying antibacterial therapy. In the absence of such data, local epidemiology and susceptibility patterns may contribute to the empiric selection of therapy.

CONTRAINDICATIONS

SPECTRACEF® is contraindicated in patients with known allergy to the cephalosporin class of antibiotics or any of its components.

SPECTRACEF® is contraindicated in patients with carnitine deficiency or inborn errors of metabolism that may result in clinically significant carnitine deficiency, because use of SPECTRACEF® causes renal excretion of carnitine. (See PRECAUTIONS, General.)

SPECTRACEF® tablets contain sodium caseinate, a milk protein. Patients with milk protein hypersensitivity (not lactose intolerance) should not be administered SPECTRACEF®.

WARNINGS

BEFORE THERAPY WITH SPECTRACEF® (CEFDITOREN PIVOXIL) IS INSTITUTED, CAREFUL INQUIRY SHOULD BE MADE TO DETERMINE WHETHER THE PATIENT HAS HAD PREVIOUS HYPERSENSITIVITY REACTIONS TO CEFDITOREN PIVOXIL, OTHER CEPHALOSPORINS, PENICILLINS, OR OTHER DRUGS. IF CEFDITOREN PIVOXIL IS TO BE GIVEN TO PENICILLIN-SENSITIVE PATIENTS, CAUTION SHOULD BE EXERCISED BECAUSE CROSS-HYPERSENSITIVITY AMONG ß-LACTAM ANTIBIOTICS HAS BEEN CLEARLY DOCUMENTED AND MAY OCCUR IN UP TO 10% OF PATIENTS WITH A HISTORY OF PENICILLIN ALLERGY. IF AN ALLERGIC REACTION TO CEFDITOREN PIVOXIL OCCURS, THE DRUG SHOULD BE DISCONTINUED. SERIOUS ACUTE HYPERSENSITIVITY REACTIONS MAY REQUIRE TREATMENT WITH EPINEPHRINE AND OTHER EMERGENCY MEASURES, INCLUDING OXYGEN, INTRAVENOUS FLUIDS, INTRAVENOUS ANTIHISTAMINES, CORTICOSTEROIDS, PRESSOR AMINES, AND AIRWAY MANAGEMENT, AS CLINICALLY INDICATED.

Pseudomembranous colitis has been reported with nearly all antibacterial agents, including cefditoren pivoxil, and may range in severity from mild to life-threatening. Therefore, it is important to consider this diagnosis in patients who present with diarrhea subsequent to the administration of antibacterial agents.

Treatment with antibacterial agents alters normal flora of the colon and may permit overgrowth of clostridia. Studies indicate that a toxin produced by Clostridium difficile (C. difficile) is a primary cause of antibiotic-associated colitis.

After the diagnosis of pseudomembranous colitis has been established, appropriate therapeutic measures should be initiated. Mild cases of pseudomembranous colitis usually respond to drug discontinuation alone. In moderate to severe cases, consideration should be given to management with fluids and electrolytes, protein supplementation, and treatment with an antibacterial drug clinically effective against C. difficile colitis.

PRECAUTIONS

General

Prescribing SPECTRACEF® in the absence of a proven or strongly suspected bacterial infection or a prophylactic indication is unlikely to provide benefit to the patient and increases the risk of the development of drug-resistant bacteria.

SPECTRACEF® is not recommended when prolonged antibiotic treatment is necessary, since other pivalate-containing compounds have caused clinical manifestations of carnitine deficiency when used over a period of months. No clinical effects of carnitine decrease have been associated with short-term treatment. The effects on carnitine concentrations of repeat short-term courses of SPECTRACEF® are not known.

In community-acquired pneumonia patients (N=192, mean age 50.3 ± 17.2 years) given a 200 mg BID regimen for 14 days, the mean decrease in serum concentrations of total carnitine while on therapy was 13.8 ± 10.8 nmole/mL, representing a 30% decrease in serum carnitine concentrations. In community-acquired pneumonia patients (N=192, mean age 51.3 ± 17.8 years) given a 400 mg BID regimen for 14 days, the mean decrease in serum concentrations of total carnitine while on therapy was 21.5 ± 13.1 mole/mL, representing a 46% decrease in serum carnitine concentrations. Plasma concentrations of carnitine returned to the normal control range within 7 days after discontinuation of cefditoren pivoxil. Comparable decreases in carnitine were observed in healthy volunteers (mean age 33.6 ± 7.4 years) following a 200 mg or 400 mg BID regimen. (See CLINICAL PHARMACOLOGY.) Community-acquired pneumonia clinical trials demonstrated no adverse events attributable to decreases in serum carnitine concentrations.

However, some sub-populations (e.g., patients with renal impairment, patients with decreased muscle mass) may be at increased risk for reductions in serum carnitine concentrations during cefditoren pivoxil therapy. Furthermore, the appropriate dose in patients with end-stage renal disease has not been determined. (See DOSAGE AND ADMINISTRATION, Patients with Renal Insufficiency).

As with other antibiotics, prolonged treatment may result in the possible emergence and overgrowth of resistant organisms. Careful observation of the patient is essential. If superinfection occurs during therapy, appropriate alternative therapy should be administered.

Cephalosporins may be associated with a fall in prothrombin activity. Those at risk include patients with renal or hepatic impairment, or poor nutritional state, as well as patients receiving a protracted course of antimicrobial therapy, and patients previously stabilized on anticoagulant therapy. Prothrombin time should be monitored in patients at risk and exogenous vitamin K administered as indicated. In clinical trials, there was no difference between cefditoren and comparator cephalosporins in the incidence of increased prothrombin time.

Information for Patients

Patients should be counseled that antibacterial drugs including SPECTRACEF® should only be used to treat bacterial infections. They do not treat viral infections (e.g., the common cold). When SPECTRACEF® is prescribed to treat a bacterial infection, patients should be told that although it is common to feel better early in the course of therapy, the medication should be taken exactly as directed. Skipping doses or not completing the full course of therapy may (1) decrease the effectiveness of the immediate treatment and (2) increase the likelihood that bacteria will develop resistance and will not be treatable by SPECTRACEF® or other antibacterial drugs in the future.

SPECTRACEF® (cefditoren pivoxil) should be taken with meals to enhance absorption.

SPECTRACEF® may be taken concomitantly with oral contraceptives.

It is not recommended that SPECTRACEF® be taken concomitantly with antacids or other drugs taken to reduce stomach acids. (See PRECAUTIONS, Drug Interactions.)

SPECTRACEF® tablets contain sodium caseinate, a milk protein. Patients with milk protein hypersensitivity (not lactose intolerance) should not be administered SPECTRACEF®.

Drug Interactions

Oral Contraceptives

Multiple doses of cefditoren pivoxil had no effect on the pharmacokinetics of ethinyl estradiol, the estrogenic component in most oral contraceptives.

Antacids

Co-administration of a single dose of an antacid which contained both magnesium (800 mg) and aluminum (900 mg) hydroxides reduced the oral absorption of a single 400 mg dose of cefditoren pivoxil administered following a meal, as evidenced by a 14% decrease in mean Cmax and an 11% decrease in mean AUC. Although the clinical significance is not known, it is not recommended that cefditoren pivoxil be taken concomitantly with antacids.

H2-Receptor Antagonists

Co-administration of a single dose of intravenously administered famotidine (20 mg) reduced the oral absorption of a single 400 mg dose of cefditoren pivoxil administered following a meal, as evidenced by a 27% decrease in mean Cmax and a 22% decrease in mean AUC. Although the clinical significance is not known, it is not recommended that cefditoren pivoxil be taken concomitantly with H2 receptor antagonists.

Probenecid

As with other ß-lactam antibiotics, co-administration of probenecid with cefditoren pivoxil resulted in an increase in the plasma exposure of cefditoren, with a 49% increase in mean Cmax, a 122% increase in mean AUC, and a 53% increase in t1/2.

Drug/Laboratory Test Interactions

Cephalosporins are known to occasionally induce a positive direct Coombs’ test. A false-positive reaction for glucose in the urine may occur with copper reduction tests (Benedict’s or Fehling’s solution or with CLINITEST® tablets), but not with enzyme-based tests for glycosuria (e.g., CLINISTIX®, TES-TAPE®). As a false-negative result may occur in the ferricyanide test, it is recommended that either the glucose oxidase or hexokinase method be used to determine blood/plasma glucose levels in patients receiving cefditoren pivoxil.

Carcinogenesis, Mutagenesis, Impairment of Fertility

No long-term animal carcinogenicity studies have been conducted with cefditoren pivoxil. Cefditoren pivoxil was not mutagenic in the Ames bacterial reverse mutation assay, or in the mouse lymphoma mutation assay at the hypoxanthineguanine phosphoribosyltransferase locus. In Chinese hamster lung cells, chromosomal aberrations were produced by cefditoren pivoxil, but not by cefditoren. Subsequent studies showed that the chromosome aberrations were due to the release of formaldehyde from the pivoxil ester moiety in the in vitro assay system. Neither cefditoren nor cefditoren pivoxil produced chromosomal aberrations when tested in an in vitro human peripheral blood lymphocyte assay, or in the in vivo mouse micronucleus assay. Cefditoren pivoxil did not induce unscheduled DNA syntheses when tested. In rats, fertility and reproduction were not affected by cefditoren pivoxil at oral doses up to 1000 mg/kg/day, approximately 24 times a human dose of 200 mg BID based on mg/m^2/day.

Pregnancy-Teratogenic Effects

Pregnancy Category B

Cefditoren pivoxil was not teratogenic up to the highest doses tested in rats and rabbits. In rats, this dose was 1000 mg/kg/day, which is approximately 24 times a human dose of 200 mg BID based on mg/m^2/day. In rabbits, the highest dose tested was 90 mg/kg/day, which is approximately four times a human dose of 200 mg BID based on mg/m^2/day. This dose produced severe maternal toxicity and resulted in fetal toxicity and abortions.

In a postnatal development study in rats, cefditoren pivoxil produced no adverse effects on postnatal survival, physical and behavioral development, learning abilities, and reproductive capability at sexual maturity when tested at doses of up to 750 mg/kg/day, the highest dose tested. This is approximately 18 times a human dose of 200 mg BID based on mg/m^2/day.

There are, however, no adequate and well-controlled studies in pregnant women. Because animal reproductive studies are not always predictive of human response, this drug should be used during pregnancy only if clearly needed.

Labor and Delivery

Cefditoren pivoxil has not been studied for use during labor and delivery.

Nursing Mothers

Cefditoren was detected in the breast milk of lactating rats. Because many drugs are excreted in human breast milk, caution should be exercised when cefditoren pivoxil is administered to nursing women.

Pediatric Use

Use of cefditoren pivoxil is not recommended for pediatric patients less than 12 years of age. The safety and efficacy of cefditoren pivoxil tablets in this population, including any effects of altered carnitine concentration, have not been established. (See PRECAUTIONS, General.)

Geriatric Use

Of the 2675 patients in clinical studies who received cefditoren pivoxil 200 mg BID, 308 (12%) were >65 years of age. Of the 2159 patients in clinical studies who received cefditoren pivoxil 400 mg BID, 307 (14%) were >65 years of age. No clinically significant differences in effectiveness or safety were observed between older and younger patients. No dose adjustments are necessary in geriatric patients with normal (for their age) renal function. This drug is known to be substantially excreted by the kidney, and the risk of toxic reactions to this drug may be greater in patients with impaired renal function. Because elderly patients are more likely to have decreased renal function, care should be taken in dose selection, and it may be useful to monitor renal function. (See DOSAGE AND ADMINISTRATION.)

ADVERSE EVENTS

Clinical Trials – SPECTRACEF® (cefditoren pivoxil) Tablets (Adults and Adolescent Patients ≥12 Years of Age)

In clinical trials, 4834 adult and adolescent patients have been treated with the recommended doses of cefditoren pivoxil tablets (200 mg or 400 mg BID). Most adverse events were mild and self-limiting. No deaths or permanent disabilities have been attributed to cefditoren.

The following adverse events were thought by the investigators to be possibly, probably, or definitely related to cefditoren tablets in multiple-dose clinical trials:

Treatment-Related Adverse Events in Trials in Adults and Adolescent Patients ≥ 12 Years of age)
 |  | SPECTRACEF |  | Comparatorsa
 |  | 200 mg BID | 400 mg BID
 |  | N=2675 | N=2159 | N=2648
Incidence ≥ | Diarhea | 11% | 15% | 8%
1% | Nausea | 4% | 6% | 5%
 | Headache | 3% | 2% | 2%
 | Abdominal Pain | 2% | 2% | 1%
 | Vaginal Moniliasis | 3%c | 6%c | 6%d
 | Dyspepsia | 1% | 2% | 2%
 | Vomiting | 1% | 1% | 2%

aincludes amoxicillin/clavulanate, cefadroxil monohydrate, cefuroxime axetil, cefpodoxime proxetil, clarithromycin, and penicillin

b1428 females

c1135 females

d1461 females

The overall incidence of adverse events, and in particular diarrhea, increased with the higher recommended dose of SPECTRACEF®.

Treatment related adverse events experienced by <1% but >0.1% of patients who received 200 mg or 400 mg BID of cefditoren pivoxil were abnormal dreams, allergic reaction, anorexia, asthenia, asthma, coagulation time increased, constipation, dizziness, dry mouth, eructation, face edema, fever, flatulence, fungal infection, gastrointestinal disorder, hyperglycemia, increased appetite, insomnia, leukopenia, leukorrhea, liver function test abnormal, myalgia, nervousness, oral moniliasis, pain, peripheral edema, pharyngitis, pseudomembranous colitis, pruritus, rash, rhinitis, sinusitis, somnolence, stomatitis, sweating, taste perversion, thirst, thrombocythemia, urticaria, and vaginitis. Pseudomembranous colitis symptoms may begin during or after antibiotic treatment. (See WARNINGS.)

Sixty-one of 2675 (2%) patients who received 200 mg BID and 69 of 2159 (3%) patients who received 400 mg BID of cefditoren pivoxil discontinued medication due to adverse events thought by the investigators to be possibly, probably, or definitely associated with cefditoren therapy. The discontinuations were primarily for gastrointestinal disturbances, usually diarrhea or nausea. Diarrhea was the reason for discontinuation in 19 of 2675 (0.7%) patients who received 200 mg BID and in 31 of 2159 (1.4%) patients who received 400 mg BID of cefditoren pivoxil.

Changes in laboratory parameters of possible clinical significance, without regard to drug relationship and which occurred in ≥1% of patients who received cefditoren pivoxil 200 mg or 400 mg BID, were hematuria (3.0% and 3.1%), increased urine white blood cells (2.3% and 2.3%), decreased hematocrit (2.1% and 2.2%), and increased glucose (1.8% and 1.1%). Those events which occurred in <1% but >0.1% of patients included the following: increased/decreased white blood cells, increased eosinophils, decreased neutrophils, increased lymphocytes, increased platelet count, decreased hemoglobin, decreased sodium, increased potassium, decreased chloride, decreased inorganic phosphorus, decreased calcium, increased SGPT/ALT, increased SGOT/AST, increased cholesterol, decreased albumin, proteinuria, and increased BUN. It is not known if these abnormalities were caused by the drug or the underlying condition being treated.

Cephalosporin Class Adverse Reactions

In addition to the adverse reactions listed above which have been observed in patients treated with cefditoren pivoxil, the following adverse reactions and altered laboratory test results have been reported for cephalosporin class antibiotics:

Adverse Reactions: Allergic reactions, anaphylaxis, drug fever, Stevens-Johnson syndrome, serum sickness-like reaction, erythema multiforme, toxic epidermal necrolysis, colitis, renal dysfunction, toxic nephropathy, reversible hyperactivity, hypertonia, hepatic dysfunction including cholestasis, aplastic anemia, hemolytic anemia, hemorrhage, and superinfection.

Altered Laboratory Tests: Prolonged prothrombin time, positive direct Coombs’ test, false-positive test for urinary glucose, elevated alkaline phosphatase, elevated bilirubin, levated LDH, increased creatinine, pancytopenia, neutropenia, and agranulocytosis.

Several cephalosporins have been implicated in triggering seizures, particularly in patients with renal impairment when the dosage was not reduced. (See DOSAGE AND ADMINISTRATION.) If seizures associated with drug therapy occur, the drug should be discontinued. Anticonvulsant therapy can be given if clinically indicated.

Postmarketing Experience

The following adverse experiences, regardless of their relationship to cefditoren pivoxil, have been reported during extensive postmarketing experience, beginning with approval in Japan in 1994: pneumonia interstitial, eosinophilic pneumonia acute, acute renal failure, arthralgia, thrombocytopenia, erythema multiforme, Stevens-Johnson Syndrome, toxic epidermal necrolysis.

OVERDOSAGE

Information on cefditoren pivoxil overdosage in humans is not available. However, with other ß-lactam antibiotics, adverse effects following overdosage have included nausea, vomiting, epigastric distress, diarrhea, and convulsions. Hemodialysis may aid in the removal of cefditoren from the body, particularly if renal function is compromised (30% reduction of plasma concentrations following 4 hours of hemodialysis). Treat overdosage symptomatically and institute supportive measures as required.

In acute animal toxicity studies, cefditoren pivoxil when tested at the limit oral doses of 5100 mg/kg in rats and up to 2000 mg/kg in dogs did not exhibit any health effects of concern. Certain effects, such as diarrhea and soft stool lasting for a few days were observed in some animals as expected with most oral antibiotics due to inhibition of intestinal microflora.

DOSAGE AND ADMINISTRATION

(See INDICATIONS AND USAGE for Indicated Pathogens.)

SPECTRACEF® (cefditoren pivoxil) Dosage and Administration* Adults and Adolescents (≥12 Years)

SPECTRACEF® (cefditoren pivoxil) Dosage and Administration* Adults and Adolescents (≥12 Years)
Type of Infection | Dosage | Duration (Days)
Community-Acquired Pneumonia | 400 mg BID | 14
Acute Bacterial Exacerbation of Chronic Bronchitis | 400 mg BID | 10
Pharyngitis/Tonsillitis | 200mg BID | 10
Uncomplicated Skin and Skin Structure Infections | 200mg BID | 10

*Should be taken with meals

Patients with Renal Insufficiency

No dose adjustment is necessary for patients with mild renal impairment (CLcr: 50-80 mL/min/1.73 m^2). It is recommended that not more than 200 mg BID be administered to patients with moderate renal impairment (CLcr: 30-49 mL/min/1.73 m^2) and 200 mg QD be administered to patients with severe renal impairment (CLcr: <30 mL/min/1.73 m^2). The appropriate dose in patients with end-stage renal disease has not been determined.

Patients with Hepatic Disease

No dose adjustments are necessary for patients with mild or moderate hepatic impairment (Child-Pugh Class A or B). The pharmacokinetics of cefditoren have not been studied in patients with severe hepatic impairment (Child-Pugh Class C).

HOW SUPPLIED

SPECTRACEF® (cefditoren pivoxil) tablets containing cefditoren pivoxil equivalent to 200 mg or 400 mg of cefditoren are available as white, elliptical, film-coated tablets imprinted with “CBP 200” or “CBP 400” in blue. These tablets are available in blister packages, as follow:

- NDC 44004-802-20: 400 mg 20 count blister pack. SPECTRACEF tablets containing cefditoren pivoxil equivalent to 400 mg of cefditoren are available as white, elliptical, film-coated tablets imprinted with “CBP 400” in blue.
- NDC 44004-802-28: 400 mg 28 count blister pack. SPECTRACEF tablets containing cefditoren pivoxil equivalent to 400 mg of cefditoren are available as white, elliptical, film-coated tablets imprinted with “CBP 400” in blue.
- NDC 44004-802-02: 400 mg 2 count blister. SPECTRACEF tablets containing cefditoren pivoxil equivalent to 400 mg of cefditoren are available as white, elliptical, film-coated tablets imprinted with “CBP 400” in blue.
- NDC 44004-801-20: 200 mg 20 count blister pack. SPECTRACEF tablets containing cefditoren pivoxil equivalent to 200 mg of cefditoren are available as white, elliptical, film-coated tablets imprinted with “CBP 200” in blue.

STORAGE

Store at 25°C (77°F); excursions permitted to 15°-30°C (59°-86°F). [See USP Controlled Room Temperature.] Protect from light and moisture. Dispense in a tight, light-resistant container.

Healthcare professionals can telephone the Medical Information Line (1-866-290-0698) for information on this product.

REFERENCES

1. National Committee for Clinical Laboratory Standards. Methods for Dilution Antimicrobial Susceptibility Tests for Bacteria That Grow Aerobically – Fifth Edition; Approved Standard, NCCLS Document M7-A5, Vol. 20, No. 2, NCCLS, Wayne, PA, January, 2000.

Rx Only

Manufactured by:

Tedec-Meiji Farma, S.A

Madrid, Spain

Distributed by:

Vansen Pharma Inc.

Westmount, QC H3Z 3C1

U.S. Patent No. 5,958,915

©2003, 2005, 2007, 2009, 2011 Vansen Pharma Inc.

CTS-001-1211-01

A233070-201207/04

PACKAGE LABEL

Spectracef 200 mg

PACKAGE LABEL

Spectracef 400 mg- 28 pack

PACKAGE LABEL

Spectracef 400 mg- 20 pack